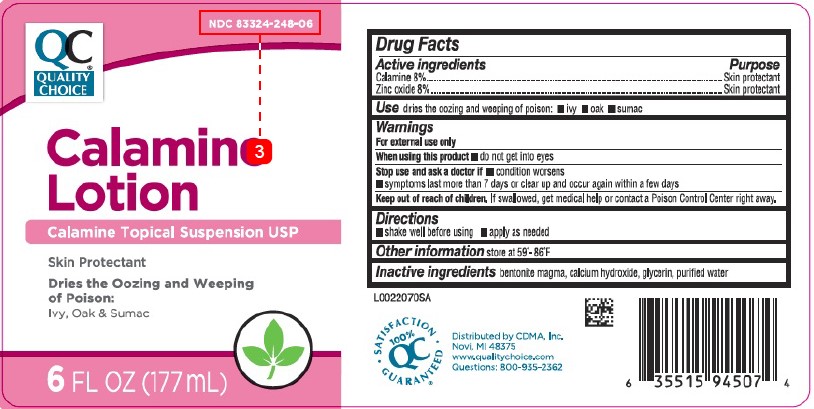 DRUG LABEL: Calamine
NDC: 83324-248 | Form: LOTION
Manufacturer: Chain Drug Marketing Association
Category: otc | Type: HUMAN OTC DRUG LABEL
Date: 20260227

ACTIVE INGREDIENTS: FERRIC OXIDE RED 80 mg/1 mL; ZINC OXIDE 80 mg/1 mL
INACTIVE INGREDIENTS: BENTONITE; CALCIUM HYDROXIDE; GLYCERIN; WATER

Quality Choice 063.001/063AA
Calamine Lotion

Active ingredients

Calamine 8%
Zinc oxide 8%

Purpose

Skin Protectant

Use

dries the oozing and weeping of poison:•ivy • oak • sumac

Warnings

For external use only

When using this product

- Do not get into eyes

Stop use and ask a doctor if

- condition worsens
- symptoms last more than 7 days or clear up and occur again within a few days

Keep out of reach of children

If swallowed, get medical help or contact a Poison Control Center right away.

Directions

- shake well before using
- apply as needed

Other information

store at 59⁰ - 86⁰ F

Inactive ingredients

bentonite magma, calcium hydroxide, glycerin, purified water

ADVERSE REACTION

Distributed by CMDA, Inc.

Novi, MI 48375

www.qualitychoice.com

Questions: 800-935-2362

SATISFACTION GUARANTEED

100% QC

PRINCIPAL DISPLAY PANEL

NDC 83324-248-06

QC

QUALITY CHOICE

Calamine

Lotion

Calamine Topical Suspension USP

Skin Protectant

Dries the Oozing and Weeping of Poison:

Ivy, Oak & Sumac

6 FL OZ (177 mL)